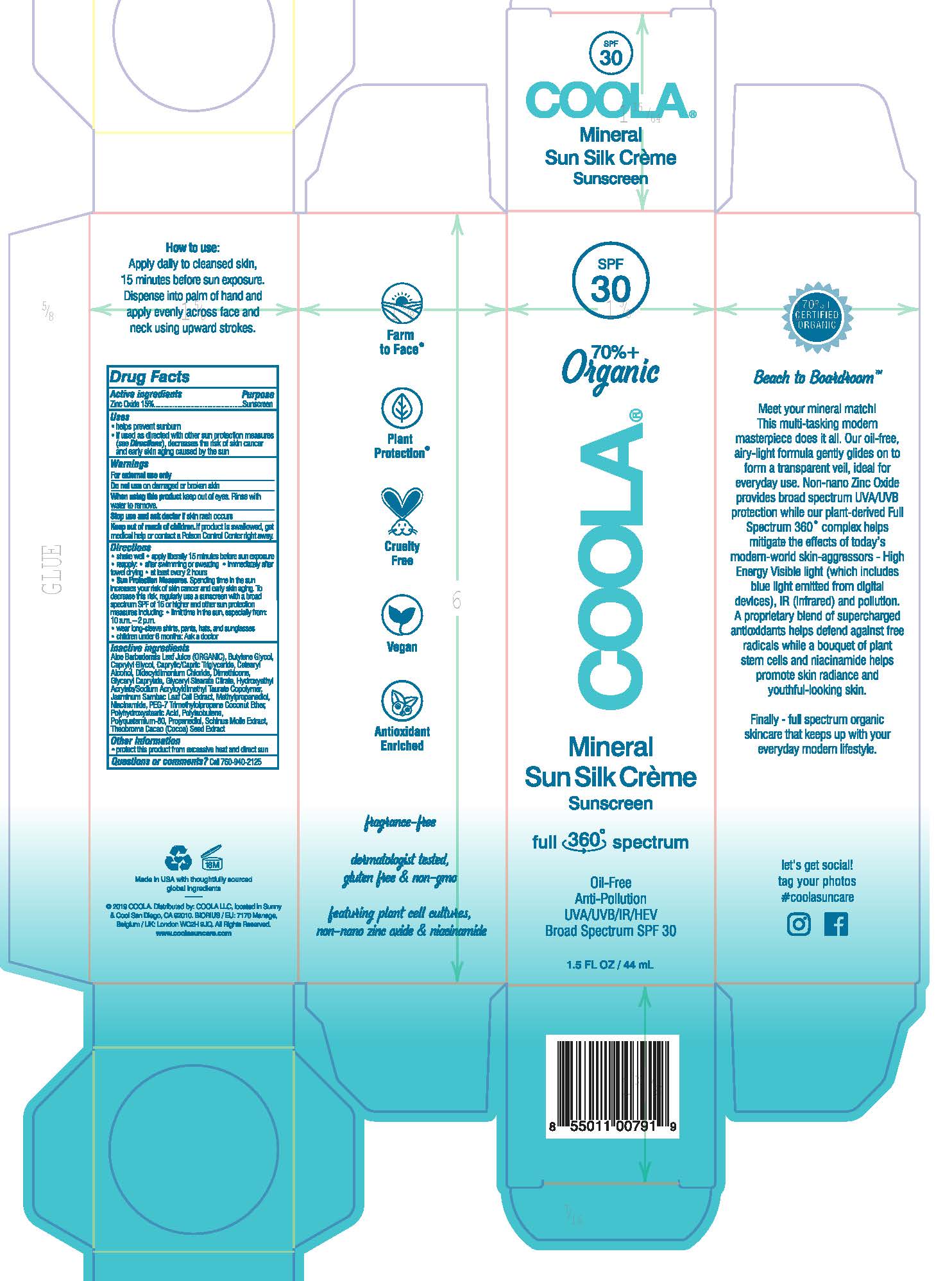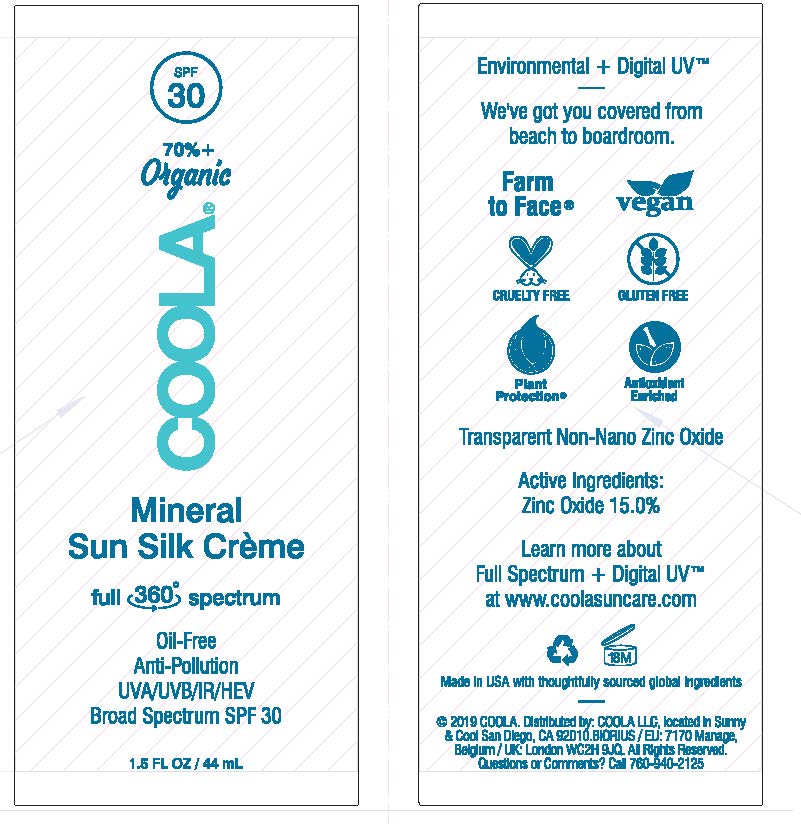 DRUG LABEL: COOLA Mineral Sun Silk Creme Sunscreen
NDC: 21839-550 | Form: LOTION
Manufacturer: GORDON LABORATORIES,INC
Category: otc | Type: HUMAN OTC DRUG LABEL
Date: 20191217

ACTIVE INGREDIENTS: ZINC OXIDE 150 mg/1 mL
INACTIVE INGREDIENTS: COCOA; SCHINUS MOLLE FRUITING TOP; POLYISOBUTYLENE (1000 MW); POLYHYDROXYSTEARIC ACID (2300 MW); NIACINAMIDE; METHYLPROPANEDIOL; JASMINUM SAMBAC FLOWER; MEDIUM-CHAIN TRIGLYCERIDES; BUTYLENE GLYCOL; SORBITAN ISOSTEARATE; PROPANEDIOL; DIDECYLDIMONIUM CHLORIDE; ALOE VERA LEAF; WATER; HYDROXYETHYL ACRYLATE/SODIUM ACRYLOYLDIMETHYL TAURATE COPOLYMER (45000 MPA.S AT 1%); DIMETHICONE; CAPRYLYL GLYCOL; CETOSTEARYL ALCOHOL; GLYCERYL CAPRYLATE; GLYCERYL STEARATE CITRATE

COOLA Mineral Sun Silk Crème Sunscreen SPF 30

DRUG FACTS

Active ingredients

Zinc Oxide 15%

Purpose

Sunscreen

Uses

* helps prevent sunburn

* if used as directed with other sun protection measures (see Directions), decreases the rise of skin cancer and early skin aging caused by the sun

Warnings

For external use only

Do not use on damaged or broken skin

When using this product keep out of eyes. Rinse with water to remove.

Stop use and ask doctor if skin rash occurs

Keep out of reach of children. If prodcut is swallowed, get medical help or contact Poison Control Center right away.

Do not use on damaged or broken skin

When using this product keep out of eyes. Rinse with water to remove

Stop use and ask doctor if skin rash occurs

Keep out of reach of children. If product is swallowed, get medical help or contact a Poison Control Center right away.

Directions

* shake well * apply liberally 15 minutes before sun exposure

* reapply: * after swimming or sweating * immediately after towel drying * at least every 2 hours

* Sun Protection Measures. Spending time in the sun increases your risk of skin cancer and early aging. To decrease this risk, regularly use a sunscreen with a broad spectrum SPF of 15 or higher and other sun protection measures including: * limit time in the sun, especially from: 10 a.m. – 2 p.m.

* wear long-sleeve shirts, pants, hats, and sunglasses

* children under 6 months: Ask a doctor

Inactive ingredients

Aloe Barbadensis Leaf Juice (ORGANIC), Butylene Glycol, Caprylyl Glycol, Caprylic/Capric Triglyceride, Cetearyl Alcohol, Didecyldimonium Chloride, Dimethicone, Glyceryl Caprylate, Glyceryl Stearate Citrate, Hydroxyethyl Acrylate/Sodium Acryloyldimethyl Taurate Copolymer, Jasminum Sambac Leaf Cell Extract, Methylpropanediol, Niacinamide, PEG-7 Trimethylolpropane Coconut Ether, Polyhydroxystearic Acid, Polyisobutene, Polyquaternium-80, Propanediol, Schinus Molle Extract, Theobroma Cacao (Cocoa) Seed Extract.

Other information

* protect this product from excessive heat and direct sun

Questions or comments? Call 760-940-2125

How to use:

Apply daily to cleansed skin,

15 minutes before sun exposure.

Dispense into palm of hand and

apply evenly across face and

neck using upward strokes,